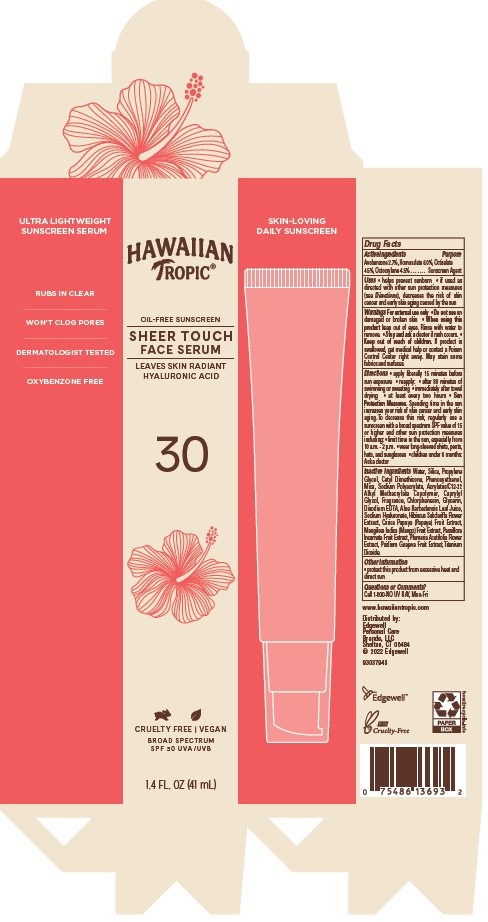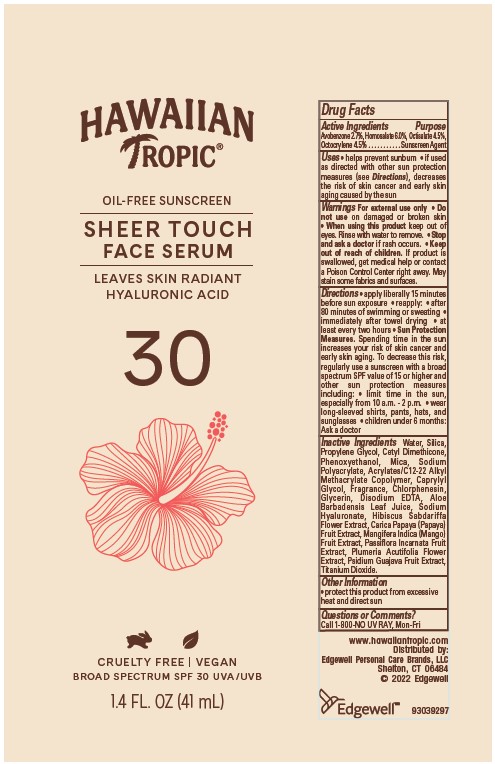 DRUG LABEL: HAWAIIAN TROPIC
NDC: 63354-209 | Form: LOTION
Manufacturer: Edgewell Personal Care Brands LLC
Category: otc | Type: HUMAN OTC DRUG LABEL
Date: 20250822

ACTIVE INGREDIENTS: AVOBENZONE 2.7 g/100 g; HOMOSALATE 6 g/100 g; OCTISALATE 4.5 g/100 g; OCTOCRYLENE 4.5 g/100 g
INACTIVE INGREDIENTS: WATER; SILICON DIOXIDE; CHLORPHENESIN; MICA; SODIUM POLYACRYLATE (2500000 MW); TITANIUM DIOXIDE; HIBISCUS SABDARIFFA FLOWER; PAPAYA; GLYCERIN; ALOE VERA LEAF; MANGO; PLUMERIA RUBRA FLOWER; PASSIFLORA INCARNATA FRUIT; PROPYLENE GLYCOL; CAPRYLYL GLYCOL; PHENOXYETHANOL; EDETATE DISODIUM

Active Ingredients

Avobenzone 2.7%, Homosalate 6.0%, Octisalate 4.5%,
Octocrylene 4.5%

Purpose

Sunscreen Agent

Uses

• helps prevent sunburn • if used as directed with other sun protection measures (see Directions), decreases the risk of skin cancer and early skin aging caused by the sun

Warnings

For external use only.

May stain some fabrics and surfaces.

Do not use

on damaged or broken skin

When using this product

keep out of eyes. Rinse with water to remove.

Stop and ask a doctor

if rash occurs.

Keep out of reach of children.

If product is swallowed, get medical help or contact a Poison Control Center right away.

Directions

• apply liberally 15 minutes before sun exposure • reapply: • after 80 minutes of swimming or sweating • immediately after towel drying • at least every two hours • Sun Protection Measures. Spending time in the sun increases your risk of skin cancer and early skin aging. To decrease this risk, regularly use a sunscreen with a broad spectrum SPF value of 15 or higher and other sun protection measures including: • limit time in the sun, especially from 10 a.m. - 2 p.m. • wear long-sleeved shirts, pants, hats, and sunglasses • children under 6 months: Ask a doctor

Inactive Ingredients

Water, Silica, Propylene Glycol, Cetyl Dimethicone, Phenoxyethanol, Mica, Sodium Polyacrylate, Acrylates/C12-22 Alkyl Methacrylate Copolymer, Caprylyl Glycol, Fragrance, Chlorphenesin, Glycerin, Disodium EDTA, Aloe Barbadensis Leaf Juice, Sodium Hyaluronate, Hibiscus Sabdariffa Flower Extract, Carica Papaya (Papaya) Fruit Extract, Mangifera Indica (Mango) Fruit Extract, Passiflora Incarnata Fruit Extract, Plumeria Acutifolia Flower Extract, Psidium Guajava Fruit Extract, Titanium Dioxide.

Other Information

• protect this product from excessive heat and direct sun

Questions or Comments?

Call 1-800-NO UV RAY, Mon-Fri

PRINCIPAL DISPLAY PANEL

HAWAIIAN TROPIC
OIL-FREE SUNSCREEN
SHEER TOUCH
FACE SERUM
LEAVES SKIN RADIANT
HYALURONIC ACID
30
CRUELTY FREE | VEGAN
BROAD SPECTRUM SPF 30 UVA/UVB
1.4 FL. OZ (41 mL)

HAWAIIAN TROPIC
OIL-FREE SUNSCREEN
SHEER TOUCH
FACE SERUM
LEAVES SKIN RADIANT
HYALURONIC ACID
30
CRUELTY FREE | VEGAN
BROAD SPECTRUM
SPF 30 UVA/UVB
1.4 FL. OZ (41 mL)